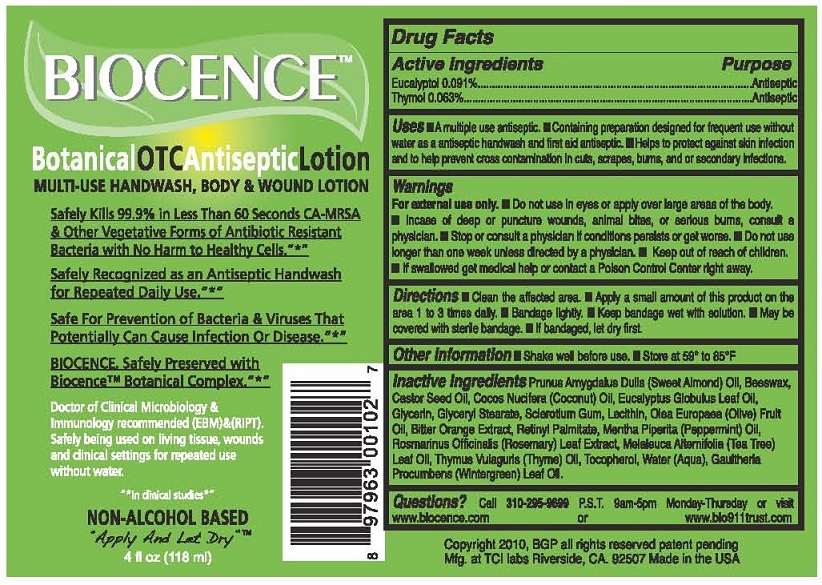 DRUG LABEL: BIOCENCE
NDC: 59998-201 | Form: LOTION
Manufacturer: Bio-Germ Protection LLC
Category: homeopathic | Type: HUMAN OTC DRUG LABEL
Date: 20251210

ACTIVE INGREDIENTS: EUCALYPTOL 0.091 g/100 mL; THYMOL 0.063 g/100 mL
INACTIVE INGREDIENTS: ALMOND OIL; YELLOW WAX; CASTOR OIL; COCONUT OIL; EUCALYPTUS GLOBULUS LEAF; GLYCERIN; GLYCERYL MONOSTEARATE; BETASIZOFIRAN; LECITHIN, SOYBEAN; OLIVE OIL; CITRUS AURANTIUM FLOWER; VITAMIN A PALMITATE; PEPPERMINT OIL; ROSMARINUS OFFICINALIS WHOLE; TEA TREE OIL; THYME OIL; TOCOPHEROL; WATER; METHYL SALICYLATE

BIOCENCE (as PLD) - BOTANICAL OTC ANTISEPTIC LOTION (59998-201)

ACTIVE INGREDIENTS

EUCALYPTOL 0.091%

THYMOL 0.063%

PURPOSE

ANTISEPTIC

USES

- A MULTIPLE USE ANTISEPTIC
- CONTAINING PREPARATION DESIGNED FOR FREQUENT USE WITHOUT WATER AS AN ANTISEPTIC HANDWASH AND FIRST AID ANTISEPTIC.
- HELPS TO PROTECT AGAINST SKIN INFECTION AND TO HELP PREVENT CROSS CONTAMINATION IN CUTS, SCRAPES, BURNS, AND OR SECONDARY INFECTIONS.

WARNINGS

FOR EXTERNAL USE ONLY.

- DO NOT USE IN EYES OR APPLY OVER LARGE AREAS OF THE BODY.
- IN CASE OF DEEP OR PUNCTURE WOUNDS, ANIMAL BITES, OR SERIOUS BURNS, CONSULT A PHYSICIAN.
- STOP OR CONSULT A PHYSICIAN IF CONDITIONS PERSIST OR GET WORSE.
- DO NOT USE LONGER THAN ONE WEEK UNLESS DIRECTED BY A PHYSICIAN.

- KEEP OUT OF REACH OF CHILDREN.
- IF SWALLOWED GET MEDICAL HELP OR CONTACT A POISON CONTROL CENTER RIGHT AWAY.

DIRECTIONS

- CLEAN THE AFFECTED AREA.
- APPLY A SMALL AMOUNT OF THIS PRODUCT ON THE AREA 1 TO 3 TIMES DAILY.
- BANDAGE LIGHTLY.
- KEEP BANDAGE WET WITH SOLUTION.
- MAY BE COVERED WITH STERILE BANDAGE.
- IF BANDAGED, LET DRY FIRST.

OTHER INFORMATION

- SHAKE WELL BEFORE USE.
- STORE AT 59° TO 85°F

INACTIVE INGREDIENTS

PRUNUS AMYGDALUS DULIS (SWEET ALMOND) OIL, BEESWAX, CASTOR SEED OIL, COCOS NUCIFERA (COCONUT) OIL, EUCALYPTUS GLOBULUS LEAF OIL, GLYCERIN, GLYCERYL STEARATE, SCLEROTIUM GUM, LECITHIN, OLEA EUROPAEA (OLIVE) FRUIT OIL, BITTER ORANGE EXTRACT, RETINYL PALMITATE, MENTHA PIPERITA (PEPPERMINT) OIL, ROSMARINUS OFFICINALIS (ROSEMARY) LEAF EXTRACT, MELALEUCA ALTERNIFOLIA (TEA TREE) LEAF OIL, THYMUS VULGARIS (THYME) OIL, TOCOPHEROL, WATER (AQUA), GAULTHERIA PROCUMBENS (WINTERGREEN) LEAF OIL.

QUESTIONS?

CALL 310-295-9699 P.S.T. 9AM - 5PM MONDAY-THURSDAY OR VISIT

WWW.BIOCENCE.COM OR WWW.BIO911TRUST.COM